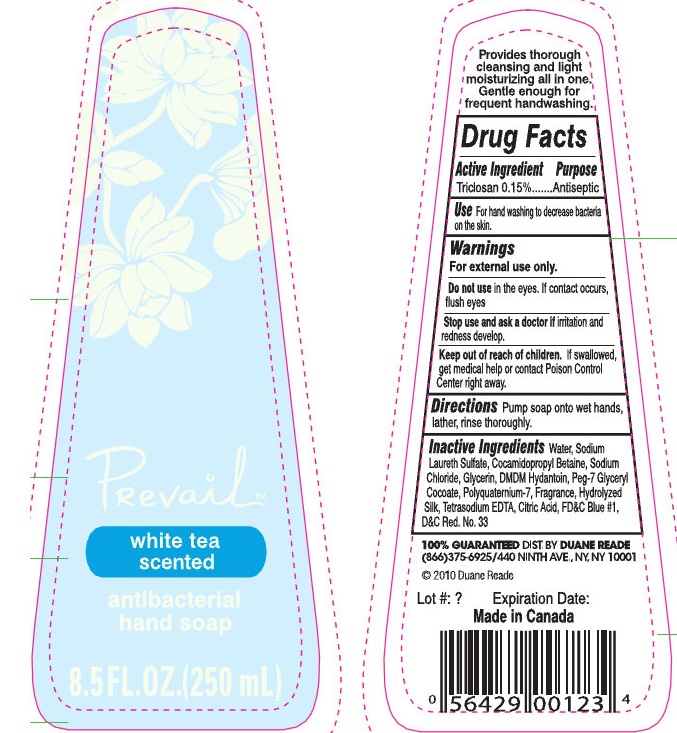 DRUG LABEL: Prevail White Tea Scented Antibacterial Hand
NDC: 67732-100 | Form: SOAP
Manufacturer: Duane Reade
Category: otc | Type: HUMAN OTC DRUG LABEL
Date: 20110225

ACTIVE INGREDIENTS: TRICLOSAN 0.15 L/100 L
INACTIVE INGREDIENTS: WATER; SODIUM LAURETH SULFATE; COCAMIDOPROPYL BETAINE; SODIUM CHLORIDE; GLYCERIN; DMDM HYDANTOIN; GLYCERYL COCOATE; BOMBYX MORI FIBER; EDETATE SODIUM; CITRIC ACID MONOHYDRATE; FD&C BLUE NO. 1; D&C RED NO. 33

Prevail White Tea Scented Antibacterial Hand Soap

Active Ingredient

Triclosan 0.15%

Purpose

Antiseptic

INDICATIONS AND USAGE

Use For hand washing to decrease bacteria on the skin.

Warnings

For external use only.

Do not use in eyes. If contact occurs, flush eyes.

Stop use and ask a doctor if irritation and redness develop.

Keep out of reach of children. If swallowed, get medical help or contact Poison Control Center right away.

DOSAGE AND ADMINISTRATION

Directions Pump soap onto wet hands, lather, rinse thoroughly.

INACTIVE INGREDIENT

Inactive ingredients Water, Sodium Laureth Sulfate, Cocamidopropyl Betaine, Sodium Chloride, Glycerin, DMDM Hydantoin, Peg-7 Glyceryl Cocoate, Polyquaternium-7, Fragrance, Hydrolyzed Silk, Tetrasodium EDTA, Citric Acid, FDandC Blue 1, DandC Red No.33

100% Guaranteed DIST. BY DUANE READE

(866)375-6925/440 Ninth Ave, NY, NY 10001

Made in Canada

PACKAGE LABEL

Prevail

white tea

scented

antibacterial
hand soap
8.5 FL. OZ (250 mL)